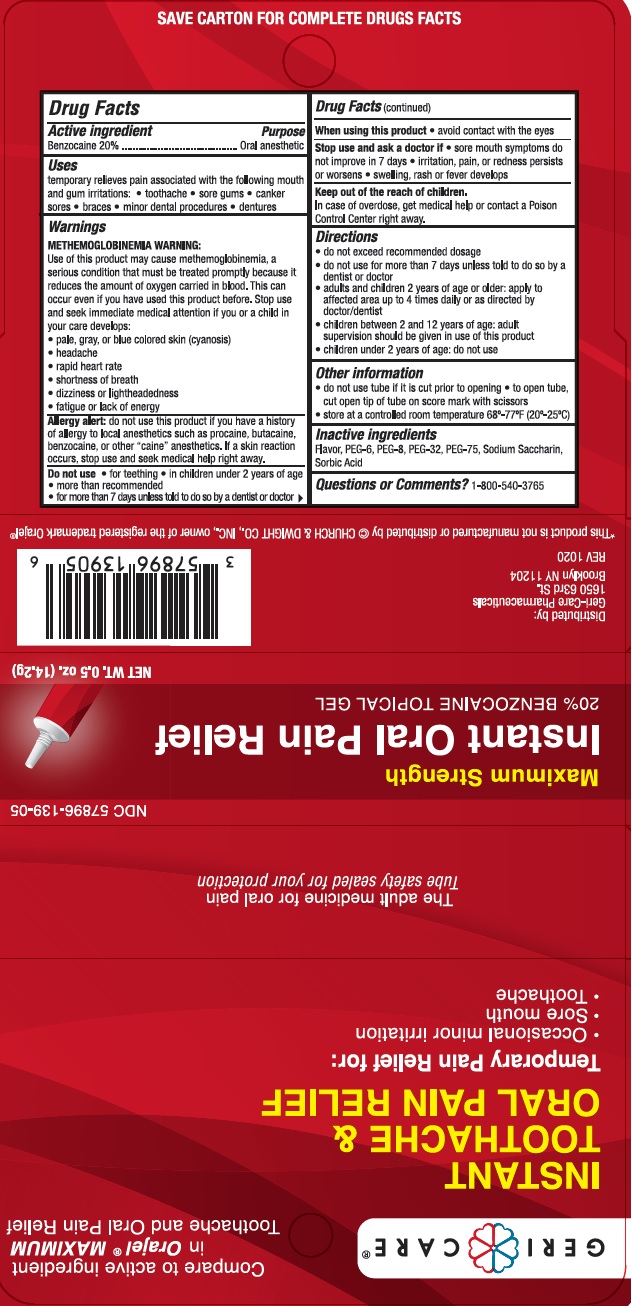 DRUG LABEL: Oral Pain Relief
NDC: 57896-139 | Form: GEL
Manufacturer: GERI-CARE PHARMACEUTICAL CORP
Category: otc | Type: HUMAN OTC DRUG LABEL
Date: 20231031

ACTIVE INGREDIENTS: BENZOCAINE 200 mg/1 g
INACTIVE INGREDIENTS: POLYETHYLENE GLYCOL 300; POLYETHYLENE GLYCOL 400; POLYETHYLENE GLYCOL 1500; POLYETHYLENE GLYCOL 3350; SACCHARIN SODIUM; SORBIC ACID

ORAL PAIN RELIEF

Drug Facts

Active Ingredient

Benzocaine 20%

Purpose

Oral anesthetic

Uses

temporary relieves pain associated with the following mouth
and gum irritations: • toothache • sore gums • canker
sores • braces • minor dental procedures • dentures

Warnings

METHEMOGLOBINEMIA WARNING:
Use of this product may cause methemoglobinemia, a
serious condition that must be treated promptly because it
reduces the amount of oxygen carried in blood. This can
occur even if you have used this product before. Stop use
and seek immediate medical attention if you or a child in
your care develops:
• pale, gray, or blue colored skin (cyanosis)
• headache
• rapid heart rate
• shortness of breath
• dizziness or lightheadedness
• fatigue or lack of energy

Allergy alert: Do not use this product if you have a history of allergy to local anesthetics such as procaine, butacaine, benzocaine or other "caine" anesthetics. If a skin reaction occurs, stop use and seek medical help right away.

Do not use

• for teething

• in children under 2 years of age

• more than recommended
• for more than 7 days unless told to do so by a dentist or doctor

When using this product

• avoid contact with the eyes

Stop use and ask a doctor if

• sore mouth symptoms do not improve in 7 days

• irritation, pain, or redness persists or worsens

• swelling, rash or fever develops

Keep out of reach of children. In case of overdose, get medical help or contact a Poison Control Center right away.

Directions

• do not exceed recommended dosage

• do not use for more than 7 days unless told to do so by a dentist or doctor

• adults and children 2 years of age or older: apply to affected area up to 4 times daily or as directed by doctor/dentist
• children between 2 and 12 years of age: adult supervision should be given in use of this product
• children under 2 years of age: do not use

Other information

• do not use tube if it is cut prior to opening

• to open tube, cut open tip of tube on score mark with scissors
• store at a controlled room temperature 68º-77ºF (20º-25ºC)

Inactive ingredients

Flavor, PEG-6, PEG-8, PEG-32, PEG-75, Sodium Saccharin, Sorbic Acid

Questions or Comments?

1-800-540-3765